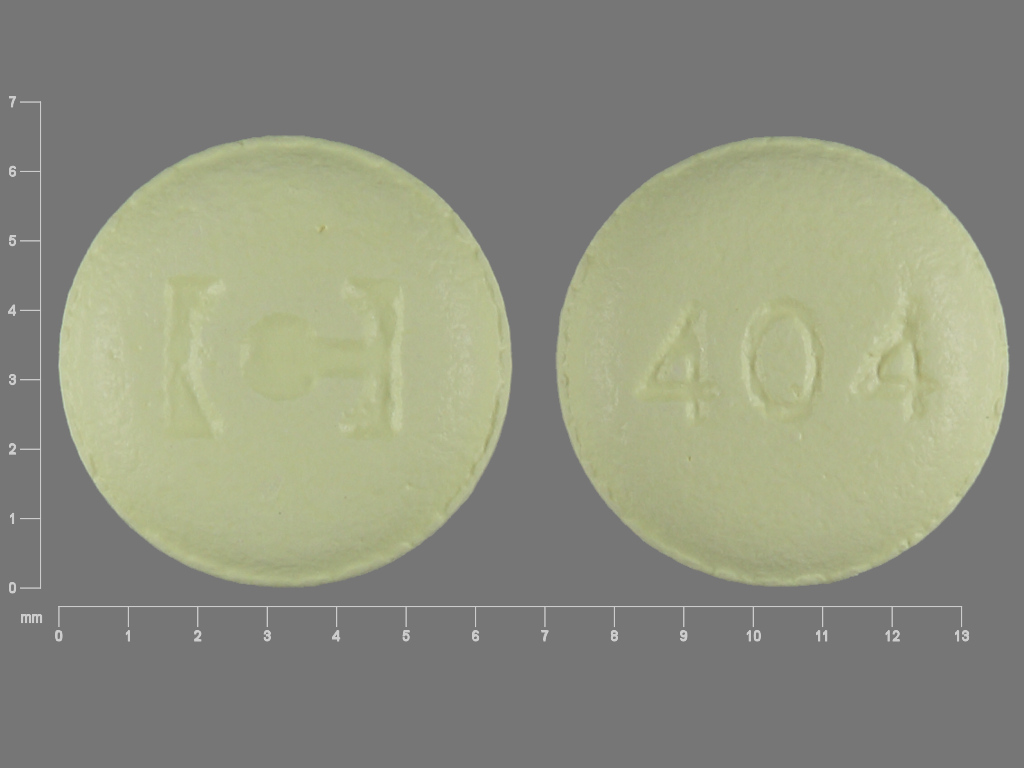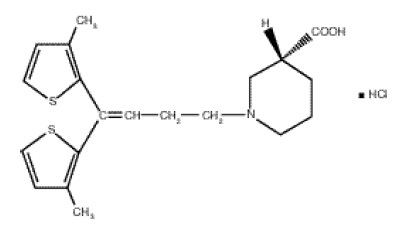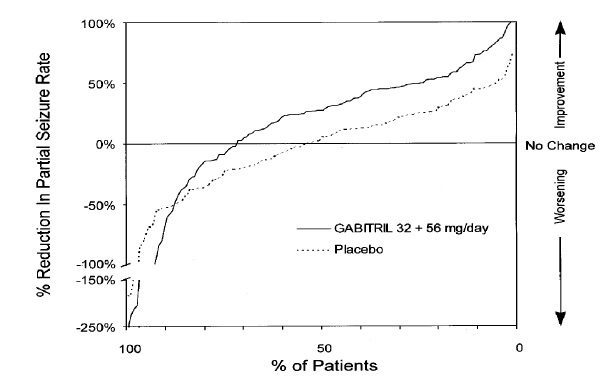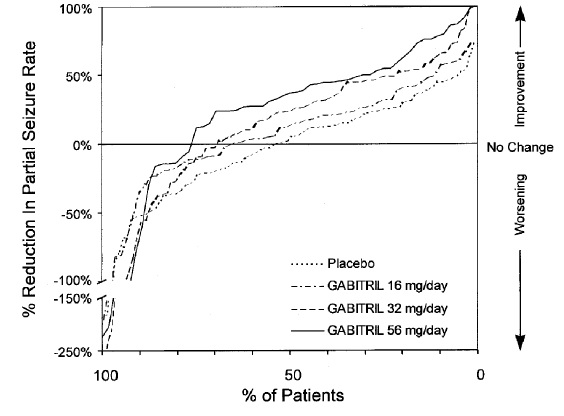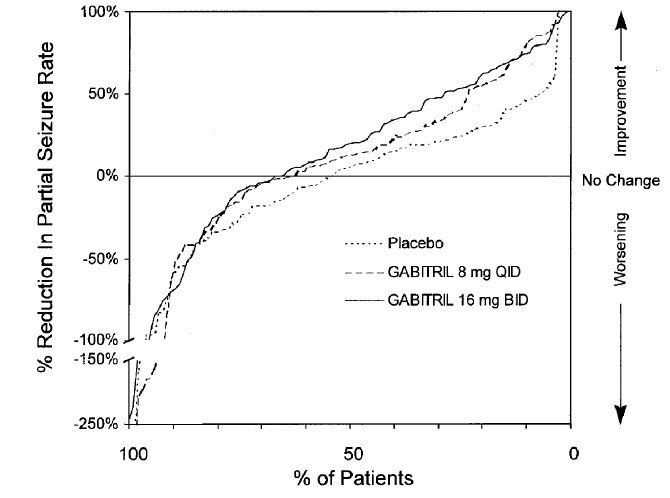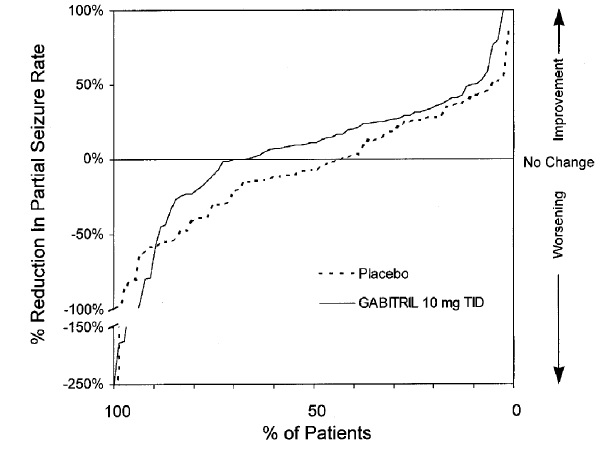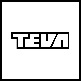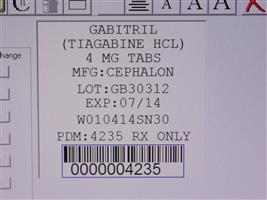 DRUG LABEL: GABITRIL
NDC: 68151-4235 | Form: TABLET, FILM COATED
Manufacturer: Carilion Materials Management
Category: prescription | Type: HUMAN PRESCRIPTION DRUG LABEL
Date: 20160806

ACTIVE INGREDIENTS: TIAGABINE HYDROCHLORIDE 4 mg/1 1
INACTIVE INGREDIENTS: ASCORBIC ACID; SILICON DIOXIDE; CROSPOVIDONE; HYDROGENATED SOYBEAN OIL; HYDROXYPROPYL CELLULOSE (TYPE H); HYPROMELLOSES; ANHYDROUS LACTOSE; MAGNESIUM STEARATE; CELLULOSE, MICROCRYSTALLINE; STARCH, CORN; STEARIC ACID; TITANIUM DIOXIDE; D&C YELLOW NO. 10

GABITRIL® (tiagabine hydrochloride) Tablets
Rx only

DESCRIPTION

GABITRIL® (tiagabine HCl) is an antiepilepsy drug available as 2 mg, 4 mg, 12 mg, and 16 mg tablets for oral administration. Its chemical name is (-)-(R)-1-[4,4-Bis(3-methyl-2-thienyl)-3-butenyl]nipecotic acid hydrochloride, its molecular formula is C20H25NO2S2 HCl, and its molecular weight is 412.0. Tiagabine HCl is a white to off-white, odorless, crystalline powder. It is insoluble in heptane, sparingly soluble in water, and soluble in aqueous base. The structural formula is:

Inactive Ingredients

GABITRIL tablets contain the following inactive ingredients: Ascorbic acid, colloidal silicon dioxide, crospovidone, hydrogenated vegetable oil wax, hydroxypropyl cellulose, hypromellose, lactose, magnesium stearate, microcrystalline cellulose, pregelatinized starch, stearic acid, and titanium dioxide.

In addition, individual tablets contain:

2 mg tablets: FD&C Yellow No. 6.

4 mg tablets: D&C Yellow No. 10.

12 mg tablets: D&C Yellow No. 10 and FD&C Blue No. 1.

16 mg tablets: FD&C Blue No. 2.

CLINICAL PHARMACOLOGY

Mechanism of Action

The precise mechanism by which tiagabine exerts its antiseizure effect is unknown, although it is believed to be related to its ability, documented in in vitro experiments, to enhance the activity of gamma aminobutyric acid (GABA), the major inhibitory neurotransmitter in the central nervous system. These experiments have shown that tiagabine binds to recognition sites associated with the GABA uptake carrier. It is thought that, by this action, tiagabine blocks GABA uptake into presynaptic neurons, permitting more GABA to be available for receptor binding on the surfaces of post-synaptic cells. Inhibition of GABA uptake has been shown for synaptosomes, neuronal cell cultures, and glial cell cultures. In rat-derived hippocampal slices, tiagabine has been shown to prolong GABA-mediated inhibitory post-synaptic potentials. Tiagabine increases the amount of GABA available in the extracellular space of the globus pallidus, ventral palladum, and substantia nigra in rats at the ED50 and ED85 doses for inhibition of pentylenetetrazol (PTZ)-induced tonic seizures. This suggests that tiagabine prevents the propagation of neural impulses that contribute to seizures by a GABA-ergic action.

Tiagabine has shown efficacy in several animal models of seizures. It is effective against the tonic phase of subcutaneous PTZ-induced seizures in mice and rats, seizures induced by the proconvulsant DMCM in mice, audiogenic seizures in genetically epilepsy-prone rats (GEPR), and amygdala-kindled seizures in rats. Tiagabine has little efficacy against maximal electroshock seizures in rats and is only partially effective against subcutaneous PTZ-induced clonic seizures in mice, picrotoxin-induced tonic seizures in the mouse, bicuculline-induced seizures in the rat, and photic seizures in photosensitive baboons. Tiagabine produces a biphasic dose-response curve against PTZ- and DMCM-induced convulsions, with attenuated effectiveness at higher doses.

Based on in vitro binding studies, tiagabine does not significantly inhibit the uptake of dopamine, norepinephrine, serotonin, glutamate, or choline and shows little or no binding to dopamine D1 and D2, muscarinic, serotonin 5HT1A, 5HT2, and 5HT3, beta-1 and 2 adrenergic, alpha-1 and alpha-2 adrenergic, histamine H2 and H3, adenosine A1 and A2, opiate µ and K1, NMDA glutamate, and GABAA receptors at 100 µM. It also lacks significant affinity for sodium or calcium channels. Tiagabine binds to histamine H1, serotonin 5HT1B, benzodiazepine, and chloride channel receptors at concentrations 20 to 400 times those inhibiting the uptake of GABA.

Pharmacokinetics

Tiagabine is well absorbed, with food slowing absorption rate but not altering the extent of absorption. The elimination half-life of tiagabine is 7 to 9 hours in normal volunteers. In epilepsy clinical trials, most patients were receiving hepatic enzyme-inducing agents (e.g., carbamazepine, phenytoin, primidone, and phenobarbital). The pharmacokinetic profile in induced patients is significantly different from the non-induced population (see PRECAUTIONS, General, Use in Non-Induced Patients). The systemic clearance of tiagabine in induced patients is approximately 60% greater resulting in considerably lower plasma concentrations and an elimination half-life of 2 to 5 hours. Given this difference in clearance, the systemic exposure after a dose of 32 mg/day in an induced population is expected to be comparable to the systemic exposure after a dose of 12 mg/day in a non-induced population. Similarly, the systemic exposure after a dose of 56 mg/day in an induced population is expected to be comparable to the systemic exposure after a dose of 22 mg/day in a non-induced population.

Absorption and Distribution: Absorption of tiagabine is rapid, with peak plasma concentrations occurring at approximately 45 minutes following an oral dose in the fasting state. Tiagabine is nearly completely absorbed (>95%), with an absolute oral bioavailability of about 90%. A high fat meal decreases the rate (mean Tmax was prolonged to 2.5 hours, and mean Cmax was reduced by about 40%) but not the extent (AUC) of tiagabine absorption. In all clinical trials, tiagabine was given with meals.

The pharmacokinetics of tiagabine are linear over the single dose range of 2 to 24 mg. Following multiple dosing, steady state is achieved within 2 days.

Tiagabine is 96% bound to human plasma proteins, mainly to serum albumin and α1-acid glycoprotein over the concentration range of 10 ng/mL to 10,000 ng/mL. While the relationship between tiagabine plasma concentrations and clinical response is not currently understood, trough plasma concentrations observed in controlled clinical trials at doses from 30 to 56 mg/day ranged from <1 ng/mL to 234 ng/mL.

Metabolism and Elimination: Although the metabolism of tiagabine has not been fully elucidated, in vivo and in vitro studies suggest that at least two metabolic pathways for tiagabine have been identified in humans: 1) thiophene ring oxidation leading to the formation of 5-oxo-tiagabine; and 2) glucuronidation. The 5-oxo-tiagabine metabolite does not contribute to the pharmacologic activity of tiagabine.

Based on in vitro data, tiagabine is likely to be metabolized primarily by the 3A isoform subfamily of hepatic cytochrome P450 (CYP 3A), although contributions to the metabolism of tiagabine from CYP 1A2, CYP 2D6 or CYP 2C19 have not been excluded.

Approximately 2% of an oral dose of tiagabine is excreted unchanged, with 25% and 63% of the remaining dose excreted into the urine and feces, respectively, primarily as metabolites, at least 2 of which have not been identified. The mean systemic plasma clearance is 109 mL/min (CV = 23%) and the average elimination half-life for tiagabine in healthy subjects ranged from 7 to 9 hours. The elimination half-life decreased by 50 to 65% in hepatic enzyme-induced patients with epilepsy compared to uninduced patients with epilepsy.

A diurnal effect on the pharmacokinetics of tiagabine was observed. Mean steady-state Cmin values were 40% lower in the evening than in the morning. Tiagabine steady-state AUC values were also found to be 15% lower following the evening tiagabine dose compared to the AUC following the morning dose.

Special Populations

Renal Insufficiency: The pharmacokinetics of total and unbound tiagabine were similar in subjects with normal renal function (creatinine clearance >80 mL/min) and in subjects with mild (creatinine clearance 40 to 80 mL/min), moderate (creatinine clearance 20 to 39 mL/min), or severe (creatinine clearance 5 to 19 mL/min) renal impairment. The pharmacokinetics of total and unbound tiagabine were also unaffected in subjects with renal failure requiring hemodialysis.

Hepatic Insufficiency: In patients with moderate hepatic impairment (Child-Pugh Class B), clearance of unbound tiagabine was reduced by about 60%. Patients with impaired liver function may require reduced initial and maintenance doses of tiagabine and/or longer dosing intervals compared to patients with normal hepatic function (see PRECAUTIONS).

Geriatric: The pharmacokinetic profile of tiagabine was similar in healthy elderly and healthy young adults.

Pediatric: Tiagabine has not been investigated in adequate and well-controlled clinical trials in patients below the age of 12. The apparent clearance and volume of distribution of tiagabine per unit body surface area or per kg were fairly similar in 25 children (age: 3 to 10 years) and in adults taking enzyme-inducing antiepilepsy drugs ([AEDs] e.g., carbamazepine or phenytoin). In children who were taking a non-inducing AED (e.g., valproate), the clearance of tiagabine based upon body weight and body surface area was 2 and 1.5-fold higher, respectively, than in non-induced adults with epilepsy.

Gender, Race and Cigarette Smoking: No specific pharmacokinetic studies were conducted to investigate the effect of gender, race and cigarette smoking on the disposition of tiagabine. Retrospective pharmacokinetic analyses, however, suggest that there is no clinically important difference between the clearance of tiagabine in males and females, when adjusted for body weight. Population pharmacokinetic analyses indicated that tiagabine clearance values were not significantly different in Caucasian (N=463), Black (N=23), or Hispanic (N=17) patients with epilepsy, and that tiagabine clearance values were not significantly affected by tobacco use.

Interactions with other Antiepilepsy Drugs: The clearance of tiagabine is affected by the co-administration of hepatic enzyme-inducing antiepilepsy drugs. Tiagabine is eliminated more rapidly in patients who have been taking hepatic enzyme-inducing drugs, e.g., carbamazepine, phenytoin, primidone and phenobarbital than in patients not receiving such treatment (see PRECAUTIONS, Drug Interactions).

Interactions with Other Drugs: See PRECAUTIONS, Drug Interactions.

CLINICAL STUDIES

The effectiveness of GABITRIL as adjunctive therapy (added to other antiepilepsy drugs) was examined in three multi-center, double-blind, placebo-controlled, parallel-group, clinical trials in 769 patients with refractory partial seizures who were taking at least one hepatic enzyme-inducing antiepilepsy drug (AED), and two placebo-controlled cross-over studies in 90 patients. In the parallel-group trials, patients had a history of at least six complex partial seizures (Study 1 and Study 2, U.S. studies), or six partial seizures of any type (Study 3, European study), occurring alone or in combination with any other seizure type within the 8-week period preceding the first study visit in spite of receiving one or more AEDs at therapeutic concentrations.

In the first two studies, the primary protocol-specified outcome measure was the median reduction from baseline in the 4-week complex partial seizure (CPS) rates during treatment. In the third study, the protocol-specified primary outcome measure was the proportion of patients achieving a 50% or greater reduction from baseline in the 4-week seizure rate of all partial seizures during treatment. The results given below include data for complex partial seizures and all partial seizures for the intent-to-treat population (all patients who received at least one dose of treatment and at least one seizure evaluation) in each study.

Study 1 was a double-blind, placebo-controlled, parallel-group trial comparing GABITRIL 16 mg/day, GABITRIL 32 mg/day, GABITRIL 56 mg/day, and placebo. Study drug was given as a four times a day regimen. After a prospective Baseline Phase of 12 weeks, patients were randomized to one of the four treatment groups described above. The 16-week Treatment Phase consisted of a 4-week Titration Period, followed by a 12-week Fixed-Dose Period, during which concomitant AED doses were held constant. The primary outcome was assessed for the combined 32 and 56 mg/day groups compared to placebo.

Study 2 was a double-blind, placebo-controlled, parallel-group trial consisting of an 8-week Baseline Phase and a 12-week Treatment Phase, the first 4 weeks of which constituted a Titration Period and the last 8 weeks a Fixed-Dose Period. This study compared GABITRIL 16 mg BID and 8 mg QID to placebo. The protocol-specified primary outcome measure was assessed separately for each group treated with GABITRIL.

The following tables display the results of the analyses of these two trials.

Table 1: Median Reduction and Median Percent Reduction from Baseline in 4-Week Seizure Rates in Study 1
 |  | Placebo; (N=91) | GABITRIL; 16 mg/day; (N=61) | GABITRIL; 32 mg/day; (N=87) | GABITRIL; 56 mg/day; (N=56) | Combined; 32 and 56; mg/day; (N=143)
Complex; Partial | Median Reduction | 0.6 | 0.8 | 2.2 [p < 0.05] | 2.9 | 2.6
Complex; Partial | Median % Reduction [Statistical significance was not assessed for median % reduction.] | 9% | 13% | 25% | 32% | 29%
All; Partial | Median Reduction | 0.2 | 1.2 | 2.7 | 3.5 | 2.9
All; Partial | Median % Reduction | 3% | 12% | 24% | 36% | 27%

Table 2: Median Reduction and Median Percent Reduction from Baseline in 4-Week Seizure Rates in Study 2
 |  | Placebo; (N=107) | GABITRIL; 16 mg BID; (N=106) | GABITRIL; 8 mg QID; (N=104)
Complex Partial | Median Reduction | 0.3 | 1.6 | 1.3 [p < 0.027, necessary for statistical significance due to multiple comparisons.]
Complex Partial | Median % Reduction [Statistical significance was not assessed for median % reduction.] | 4% | 22% | 15%
All Partial | Median Reduction | 0.5 | 1.6 | 1.3
All Partial | Median % Reduction | 5% | 19% | 13%

Figures 1 to 4 present the proportion of patients (X-axis) whose percent reduction from baseline in the all partial seizure rate was at least as great as that indicated on the Y axis in the three placebo-controlled adjunctive studies (Studies 1, 2, and 3). A positive value on the Y axis indicates an improvement from baseline (i.e., a decrease in seizure rate), while a negative value indicates a worsening from baseline (i.e., an increase in seizure rate). Thus, in a display of this type, the curve for an effective treatment is shifted to the left of the curve for placebo.

Figure 1 indicates that the proportion of patients achieving any particular level of reduction in seizure rate was consistently higher for the combined GABITRIL 32 mg and 56 mg groups compared to the placebo group in Study 1. For example, Figure 1 indicates that approximately 24% of patients treated with GABITRIL experienced a 50% or greater reduction, compared to 4% in the placebo group.

Figure 1: Study 1

Figure 2 also displays the results for Study 1, which was a dose-response study, by treatment group, without combining GABITRIL dosage groups. Figure 2 indicates a dose-response relationship across the three GABITRIL groups. The proportion of patients achieving any particular level of reduction in all partial seizure rates was consistently higher as the dose of GABITRIL was increased. For example, Figure 2 indicates that approximately 4% of patients in the placebo group experienced a 50% or greater reduction in all partial seizure rate, compared to approximately 10% of the GABITRIL 16 mg/day group, 21% of the GABITRIL 32 mg/day group, and 30% of the GABITRIL 56 mg/day group.

Figure 2: Study 1

Figure 3 indicates that the proportion of patients achieving any particular level of reduction in partial seizure rate was consistently greater in patients taking GABITRIL than in those taking placebo in Study 2 (Study 2 compared placebo to GABITRIL 32 mg/day; one of the GABITRIL groups received 8 mg QID, while the other GABITRIL group received 16 mg BID). For example, Figure 3 indicates that approximately 7% of patients in the placebo group experienced a 50% or greater reduction in their partial seizure rate, compared to approximately 23% of patients in the GABITRIL 8 mg QID group and 28% of patients in the GABITRIL 16 mg BID group.

Figure 3: Study 2

Study 3 was a double-blind, placebo-controlled, parallel-group trial that compared GABITRIL 10 mg TID (N=77) with placebo (N=77). In this trial, patients were followed prospectively during a 12-week Baseline Phase and then randomized to receive study drug during an 18-week Treatment Phase. During the first 6 weeks of treatment (Titration Period), patients were titrated to 30 mg/day, after which they were maintained on this dose during the 12-week Fixed-Dose Period. The protocol-specified primary outcome measure (proportion of patients who achieved at least a 50% reduction from baseline in partial seizure rate) did not reach statistical significance. However, analyses of the median reduction from baseline in 4-week partial seizure rate (the analyses presented above for Study 1 and Study 2) were performed and showed a statistically significant improvement compared to placebo in all partial and complex partial seizure rates (Table 3):

Table 3: Median Reduction and Median Percent Reduction from Baseline in 4-Week Seizure Rates in Study 3
 |  | Placebo; (N=77) | GABITRIL; 30 mg/day; (N=77)
Complex Partial [N=72 and 75 for placebo and GABITRIL, respectively.] | Median Reduction | -0.1 | 1.3 [p < 0.05]
Complex Partial [N=72 and 75 for placebo and GABITRIL, respectively.] | Median % Reduction [Statistical significance was not assessed for median % reduction.] | -1% | 14%
All Partial | Median Reduction | -0.5 | 1.1
All Partial | Median % Reduction | -7% | 11%

Figure 4 indicates that the proportion of patients achieving any particular level of reduction in seizure activity was consistently higher in those taking GABITRIL than those taking placebo in Study 3. For example, Figure 4 indicates that approximately 5% of patients in the placebo group experienced a 50% or greater reduction in their partial seizure rate compared to approximately 10% of patients in the GABITRIL group.

Figure 4: Study 3

The two other placebo-controlled trials that examined the effectiveness of GABITRIL were small cross-over trials (N=46 and 44). Both trials included an open Screening Phase during which patients were titrated to an optimal dose and then treated with this dose for an additional 4 weeks. After this Open Phase, patients were randomized to one of two blinded treatment sequences (GABITRIL followed by placebo or placebo followed by GABITRIL). The Double-Blind Phase consisted of two Treatment Periods, each lasting 7 weeks (with a 3 week washout between periods). The outcome measures were median with-in patient differences between placebo and GABITRIL Treatment Periods in 4-week complex partial and all partial seizure rates. The reductions in seizure rates were statistically significant in both studies.

INDICATIONS AND USAGE

GABITRIL (tiagabine hydrochloride) is indicated as adjunctive therapy in adults and children 12 years and older in the treatment of partial seizures.

CONTRAINDICATIONS

GABITRIL is contraindicated in patients who have demonstrated hypersensitivity to the drug or its ingredients.

WARNINGS

Seizures in Patients Without Epilepsy: Post-marketing reports have shown that GABITRIL use has been associated with new onset seizures and status epilepticus in patients without epilepsy. Dose may be an important predisposing factor in the development of seizures, although seizures have been reported in patients taking daily doses of GABITRIL as low as 4 mg/day. In most cases, patients were using concomitant medications (antidepressants, antipsychotics, stimulants, narcotics) that are thought to lower the seizure threshold. Some seizures occurred near the time of a dose increase, even after periods of prior stable dosing.

The GABITRIL dosing recommendations in current labeling for treatment of epilepsy were based on use in patients with partial seizures 12 years of age and older, most of whom were taking enzyme-inducing antiepileptic drugs (AEDs; e.g., carbamazepine, phenytoin, primidone and phenobarbital) which lower plasma levels of GABITRIL by inducing its metabolism. Use of GABITRIL without enzyme-inducing antiepileptic drugs results in blood levels about twice those attained in the studies on which current dosing recommendations are based (see DOSAGE AND ADMINISTRATION).

Safety and effectiveness of GABITRIL have not been established for any indication other than as adjunctive therapy for partial seizures in adults and children 12 years and older.

In nonepileptic patients who develop seizures while on GABITRIL treatment, GABITRIL should be discontinued and patients should be evaluated for an underlying seizure disorder.

Seizures and status epilepticus are known to occur with GABITRIL overdosage (see OVERDOSAGE).

Suicidal Behavior and Ideation: Antiepileptic drugs (AEDs), including GABITRIL, increase the risk of suicidal thoughts or behavior in patients taking these drugs for any indication. Patients treated with any AED for any indication should be monitored for the emergence or worsening of depression, suicidal thoughts or behavior, and/or any unusual changes in mood or behavior.

Pooled analyses of 199 placebo-controlled clinical trials (mono- and adjunctive therapy) of 11 different AEDs showed that patients randomized to one of the AEDs had approximately twice the risk (adjusted Relative Risk 1.8, 95% CI:1.2, 2.7) of suicidal thinking or behavior compared to patients randomized to placebo. In these trials, which had a median treatment duration of 12 weeks, the estimated incidence rate of suicidal behavior or ideation among 27,863 AED-treated patients was 0.43%, compared to 0.24% among 16,029 placebo-treated patients, representing an increase of approximately one case of suicidal thinking or behavior for every 530 patients treated. There were four suicides in drug-treated patients in the trials and none in placebo-treated patients, but the number is too small to allow any conclusion about drug effect on suicide.

The increased risk of suicidal thoughts or behavior with AEDs was observed as early as one week after starting drug treatment with AEDs and persisted for the duration of treatment assessed. Because most trials included in the analysis did not extend beyond 24 weeks, the risk of suicidal thoughts or behavior beyond 24 weeks could not be assessed.

The risk of suicidal thoughts or behavior was generally consistent among drugs in the data analyzed. The finding of increased risk with AEDs of varying mechanisms of action and across a range of indications suggests that the risk applies to all AEDs used for any indication. The risk did not vary substantially by age (5-100 years) in the clinical trials analyzed.

Table 4 shows absolute and relative risk by indication for all evaluated AEDs.

Table 4: Risk by Indication for Antiepileptic Drugs in the Pooled Analysis
Indication | Placebo Patients with Events per 1000 Patients | Drug Patients with Events per 1000 Patients | Relative Risk: Incidence of Events in Drug Patients/Incidence in Placebo Patients | Risk Difference: Additional Drug Patients with Events per 1000 Patients
Epilepsy | 1.0 | 3.4 | 3.5 | 2.4
Psychiatric | 5.7 | 8.5 | 1.5 | 2.9
Other | 1.0 | 1.8 | 1.9 | 0.9
Total | 2.4 | 4.3 | 1.8 | 1.9

The relative risk for suicidal thoughts or behavior was higher in clinical trials for epilepsy than in clinical trials for psychiatric or other conditions, but the absolute risk differences were similar for the epilepsy and psychiatric indications.

Anyone considering prescribing GABITRIL or any other AED must balance the risk of suicidal thoughts or behavior with the risk of untreated illness. Epilepsy and many other illnesses for which AEDs are prescribed are themselves associated with morbidity and mortality and an increased risk of suicidal thoughts and behavior. Should suicidal thoughts and behavior emerge during treatment, the prescriber needs to consider whether the emergence of these symptoms in any given patient may be related to the illness being treated.

Patients, their caregivers, and families should be informed that AEDs increase the risk of suicidal thoughts and behavior and should be advised of the need to be alert for the emergence or worsening of the signs and symptoms of depression, any unusual changes in mood or behavior, or the emergence of suicidal thoughts, behavior, or thoughts about self-harm. Behaviors of concern should be reported immediately to healthcare providers.

Withdrawal Seizures: As a rule, antiepilepsy drugs should not be abruptly discontinued because of the possibility of increasing seizure frequency. In a placebo-controlled, double-blind, dose-response study (Study 1 described in CLINICAL STUDIES) designed, in part, to investigate the capacity of GABITRIL to induce withdrawal seizures, study drug was tapered over a 4-week period after 16 weeks of treatment. Patients’ seizure frequency during this 4-week withdrawal period was compared to their baseline seizure frequency (before study drug). For each partial seizure type, for all partial seizure types combined, and for secondarily generalized tonic-clonic seizures, more patients experienced increases in their seizure frequencies during the withdrawal period in the three GABITRIL groups than in the placebo group. The increase in seizure frequency was not affected by dose. GABITRIL should be withdrawn gradually to minimize the potential of increased seizure frequency, unless safety concerns require a more rapid withdrawal.

Cognitive/Neuropsychiatric Adverse Events: Adverse events most often associated with the use of GABITRIL were related to the central nervous system. The most significant of these can be classified into 2 general categories: 1) impaired concentration, speech or language problems, and confusion (effects on thought processes); and 2) somnolence and fatigue (effects on level of consciousness). The majority of these events were mild to moderate. In controlled clinical trials, these events led to discontinuation of treatment with GABITRIL in 6% (31 of 494) of patients compared to 2% (5 of 275) of the placebo-treated patients. A total of 1.6% (8 of 494) of the GABITRIL treated patients in the controlled trials were hospitalized secondary to the occurrence of these events compared to 0% of the placebo treated patients. Some of these events were dose related and usually began during initial titration.

Patients with a history of spike and wave discharges on EEG have been reported to have exacerbations of their EEG abnormalities associated with these cognitive/neuropsychiatric events. This raises the possibility that these clinical events may, in some cases, be a manifestation of underlying seizure activity (see PRECAUTIONS, Laboratory Tests, EEG). In the documented cases of spike and wave discharges on EEG with cognitive/neuropsychiatric events, patients usually continued tiagabine, but required dosage adjustment.

Additionally, there have been postmarketing reports of patients who have experienced cognitive/neuropsychiatric symptoms, some accompanied by EEG abnormalities such as generalized spike and wave activity, that have been reported as nonconvulsant status epilepticus. Some reports describe recovery following reduction of dose or discontinuation of GABITRIL.

Status Epilepticus: In the three double-blind, placebo-controlled, parallel-group studies (Studies 1, 2, and 3), the incidence of any type of status epilepticus (simple, complex, or generalized tonic-clonic) in patients receiving GABITRIL was 0.8% (4 of 494 patients) versus 0.7% (2 of 275 patients) receiving placebo. Among the patients treated with GABITRIL across all epilepsy studies (controlled and uncontrolled), 5% had some form of status epilepticus. Of the 5%, 57% of patients experienced complex partial status epilepticus. A critical risk factor for status epilepticus was the presence of a previous history; 33% of patients with a history of status epilepticus had recurrence during GABITRIL treatment. Because adequate information about the incidence of status epilepticus in a similar population of patients with epilepsy who have not received treatment with GABITRIL is not available, it is impossible to state whether or not treatment with GABITRIL is associated with a higher or lower rate of status epilepticus than would be expected to occur in a similar population not treated with GABITRIL.

Sudden Unexpected Death In Epilepsy (SUDEP): There have been as many as 10 cases of sudden unexpected deaths during the clinical development of tiagabine among 2531 patients with epilepsy (3831 patient-years of exposure).

This represents an estimated incidence of 0.0026 deaths per patient-year. This rate is within the range of estimates for the incidence of sudden and unexpected deaths in patients with epilepsy not receiving GABITRIL (ranging from 0.0005 for the general population with epilepsy, 0.003 to 0.004 for clinical trial populations similar to that in the clinical development program for GABITRIL, to 0.005 for patients with refractory epilepsy). The estimated SUDEP rates in patients receiving GABITRIL are also similar to those observed in patients receiving other antiepilepsy drugs, chemically unrelated to GABITRIL, that underwent clinical testing in similar populations at about the same time. This evidence suggests that the SUDEP rates reflect population rates, not a drug effect.

PRECAUTIONS

General

Use in Non-Induced Patients: Virtually all experience with GABITRIL has been obtained in patients with epilepsy receiving at least one concomitant enzyme-inducing antiepilepsy drug (AED), which lowers the plasma levels of tiagabine. Use in non-induced patients requires lower doses of GABITRIL. These patients may also require a slower titration of GABITRIL compared to that of induced patients (see DOSAGE AND ADMINISTRATION). Patients taking a combination of inducing and non-inducing agents (e.g., carbamazepine and valproate) should be considered to be induced. Patients not receiving hepatic enzyme-inducing agents are referred to as non-induced patients.

Generalized Weakness: Moderately severe to incapacitating generalized weakness has been reported following administration of GABITRIL in 28 of 2531 (approximately 1%) patients with epilepsy. The weakness resolved in all cases after a reduction in dose or discontinuation of GABITRIL.

Binding in the Eye and Other Melanin-Containing Tissues: When dogs received a single dose of radiolabeled tiagabine, there was evidence of residual binding in the retina and uvea after 3 weeks (the latest time point measured). Although not directly measured, melanin binding is suggested. The ability of available tests to detect potentially adverse consequences, if any, of the binding of tiagabine to melanin-containing tissue is unknown and there was no systematic monitoring for relevant ophthalmological changes during the clinical development of GABITRIL. However, long term (up to one year) toxicological studies of tiagabine in dogs showed no treatment-related ophthalmoscopic changes and macro- and microscopic examinations of the eye were unremarkable. Accordingly, although there are no specific recommendations for periodic ophthalmologic monitoring, prescribers should be aware of the possibility of long-term ophthalmologic effects.

Use in Hepatically-Impaired Patients: Because the clearance of tiagabine is reduced in patients with liver disease, dosage reduction may be necessary in these patients.

Serious Rash: Four patients treated with tiagabine during the product’s premarketing clinical testing developed what were considered to be serious rashes. In two patients, the rash was described as maculopapular; in one it was described as vesiculobullous; and in the 4th case, a diagnosis of Stevens Johnson syndrome was made. In none of the 4 cases is it certain that tiagabine was the primary, or even a contributory, cause of the rash. Nevertheless, drug associated rash can, if extensive and serious, cause irreversible morbidity, even death.

Information for Patients

Patients should be informed of the availability of a Medication Guide, and they should be instructed to read it prior to taking GABITRIL. The complete text of the Medication Guide is provided at the end of this labeling.

Suicidal Thinking and Behavior - Patients, their caregivers, and families should be counseled that AEDs, including GABITRIL, may increase the risk of suicidal thoughts and behavior and should be advised of the need to be alert for the emergence or worsening of symptoms of depression, any unusual changes in mood or behavior, or the emergence of suicidal thoughts, behavior, or thoughts about self-harm. Behaviors of concern should be reported immediately to healthcare providers.

Patients should be advised that GABITRIL may cause dizziness, somnolence, and other symptoms and signs of CNS depression. Accordingly, patients should be advised neither to drive nor to operate other complex machinery until they have gained sufficient experience on GABITRIL to gauge whether or not it affects their mental and/or motor performance adversely. Because of the possible additive depressive effects, caution should also be used when patients are taking other CNS depressants in combination with GABITRIL.

Because teratogenic effects were seen in the offspring of rats exposed to maternally toxic doses of tiagabine and because experience in humans is limited, patients should be advised to notify their physicians if they become pregnant or intend to become pregnant during therapy.

Because of the possibility that tiagabine may be excreted in breast milk, patients should be advised to notify those providing care to themselves and their children if they intend to breast-feed or are breast-feeding an infant.

Patients should be encouraged to enroll in the North American Antiepileptic Drug (NAAED) Pregnancy Registry if they become pregnant. This registry is collecting information about the safety of antiepileptic drugs during pregnancy. To enroll, patients can call the toll free number 1-888-233-2334 (see PRECAUTIONS, Pregnancy).

Laboratory Tests

Therapeutic Monitoring of Plasma Concentrations of Tiagabine: A therapeutic range for tiagabine plasma concentrations has not been established. In controlled trials, trough plasma concentrations observed among patients randomized to doses of tiagabine that were statistically significantly more effective than placebo ranged from <1 ng/mL to 234 ng/mL (median, 10 th and 90th percentiles are 23.7 ng/mL, 5.4 ng/mL, and 69.8 ng/mL, respectively). Because of the potential for pharmacokinetic interactions between GABITRIL and drugs that induce or inhibit hepatic metabolizing enzymes, it may be useful to obtain plasma levels of tiagabine before and after changes are made in the therapeutic regimen.

Clinical Chemistry and Hematology: During the development of GABITRIL, no systematic abnormalities on routine laboratory testing were noted. Therefore, no specific guidance is offered regarding routine monitoring; the practitioner retains responsibility for determining how best to monitor the patient in his/her care.

EEG: Patients with a history of spike and wave discharges on EEG have been reported to have exacerbations of their EEG abnormalities associated with cognitive/neuropsychiatric events. This raises the possibility that these clinical events may, in some cases, be a manifestation of underlying seizure activity (see WARNINGS, Cognitive/Neuropsychiatric Adverse Events). In the documented cases of spike and wave discharges on EEG with cognitive/neuropsychiatric events, patients usually continued tiagabine, but required dosage adjustment.

Drug Interactions

In evaluating the potential for interactions among co-administered antiepilepsy drugs (AEDs), whether or not an AED induces or does not induce metabolic enzymes is an important consideration. Carbamazepine, phenytoin, primidone, and phenobarbital are generally classified as enzyme inducers; valproate and gabapentin are not. GABITRIL is considered to be a non-enzyme inducing AED (see PRECAUTIONS, General, Use in Non-Induced Patients).

The drug interaction data described in this section were obtained from studies involving either healthy subjects or patients with epilepsy.

Effects of GABITRIL on other Antiepilepsy Drugs (AEDs):

Phenytoin: Tiagabine had no effect on the steady-state plasma concentrations of phenytoin in patients with epilepsy.

Carbamazepine: Tiagabine had no effect on the steady-state plasma concentrations of carbamazepine or its epoxide metabolite in patients with epilepsy.

Valproate: Tiagabine causes a slight decrease (about 10%) in steady-state valproate concentrations.

Phenobarbital or Primidone: No formal pharmacokinetic studies have been performed examining the addition of tiagabine to regimens containing phenobarbital or primidone. The addition of tiagabine in a limited number of patients in three well-controlled studies caused no systematic changes in phenobarbital or primidone concentrations when compared to placebo.

Effects of other Antiepilepsy Drugs (AEDs) on GABITRIL:

Carbamazepine: Population pharmacokinetic analyses indicate that tiagabine clearance is 60% greater in patients taking carbamazepine with or without other enzyme-inducing AEDs.

Phenytoin: Population pharmacokinetic analyses indicate that tiagabine clearance is 60% greater in patients taking phenytoin with or without other enzyme-inducing AEDs.

Phenobarbital (Primidone): Population pharmacokinetic analyses indicate that tiagabine clearance is 60% greater in patients taking phenobarbital (primidone) with or without other enzyme-inducing AEDs.

Valproate: The addition of tiagabine to patients taking valproate chronically had no effect on tiagabine pharmacokinetics, but valproate significantly decreased tiagabine binding in vitro from 96.3 to 94.8%, which resulted in an increase of approximately 40% in the free tiagabine concentration. The clinical relevance of this in vitro finding is unknown.

Interaction of GABITRIL with Other Drugs:

Cimetidine: Co-administration of cimetidine (800 mg/day) to patients taking tiagabine chronically had no effect on tiagabine pharmacokinetics.

Theophylline: A single 10 mg dose of tiagabine did not affect the pharmacokinetics of theophylline at steady state.

Warfarin: No significant differences were observed in the steady-state pharmacokinetics of R-warfarin or S-warfarin with the addition of tiagabine given as a single dose. Prothrombin times were not affected by tiagabine.

Digoxin: Concomitant administration of tiagabine did not affect the steady-state pharmacokinetics of digoxin or the mean daily trough serum level of digoxin.

Ethanol or Triazolam: No significant differences were observed in the pharmacokinetics of triazolam (0.125 mg) and tiagabine (10 mg) when given together as a single dose. The pharmacokinetics of ethanol were not affected by multiple-dose administration of tiagabine. Tiagabine has shown no clinically important potentiation of the pharmacodynamic effects of triazolam or alcohol. Because of the possible additive effects of drugs that may depress the nervous system, ethanol or triazolam should be used cautiously in combination with tiagabine.

Oral Contraceptives: Multiple dose administration of tiagabine (8 mg/day monotherapy) did not alter the pharmacokinetics of oral contraceptives in healthy women of child-bearing age.

Antipyrine: Antipyrine pharmacokinetics were not significantly different before and after tiagabine multiple-dose regimens. This indicates that tiagabine does not cause induction or inhibition of the hepatic microsomal enzyme systems responsible for the metabolism of antipyrine.

Interaction of GABITRIL with Highly Protein Bound Drugs:

In vitro data showed that tiagabine is 96% bound to human plasma protein and therefore has the potential to interact with other highly protein bound compounds. Such an interaction can potentially lead to higher free fractions of either tiagabine or the competing drug.

Carcinogenesis, Mutagenesis, Impairment of Fertility

Carcinogenesis: In rats, a study of the potential carcinogenicity associated with tiagabine HCl administration showed that 200 mg/kg/day (plasma exposure [AUC] 36 to 100 times that at the maximum recommended human dosage [MRHD] of 56 mg/day) for 2 years resulted in small, but statistically significant increases in the incidences of hepatocellular adenomas in females and Leydig cell tumors of the testis in males. The significance of these findings relative to the use of GABITRIL in humans is unknown. The no effect dosage for induction of tumors in this study was 100 mg/kg/day (17 to 50 times the exposure at the MRHD). No statistically significant increases in tumor formation were noted in mice at dosages up to 250 mg/kg/day (20 times the MRHD on a mg/m^2 basis).

Mutagenesis: Tiagabine produced an increase in structural chromosome aberration frequency in human lymphocytes in vitro in the absence of metabolic activation. No increase in chromosomal aberration frequencies was demonstrated in this assay in the presence of metabolic activation. No evidence of genetic toxicity was found in the in vitro bacterial gene mutation assays, the in vitro HGPRT forward mutation assay in Chinese hamster lung cells, the in vivo mouse micronucleus test, or an unscheduled DNA synthesis assay.

Impairment of Fertility: Studies of male and female rats administered dosages of tiagabine HCl prior to and during mating, gestation, and lactation have shown no impairment of fertility at doses up to 100 mg/kg/day. This dose represents approximately 16 times the maximum recommended human dose (MRHD) of 56 mg/day, based on body surface area (mg/m^2). Lowered maternal weight gain and decreased viability and growth in the rat pups were found at 100 mg/kg, but not at 20 mg/kg/day (3 times the MRHD on a mg/m^2 basis).

Pregnancy:

Pregnancy Category C: Tiagabine has been shown to have adverse effects on embryo-fetal development, including teratogenic effects, when administered to pregnant rats and rabbits at doses greater than the human therapeutic dose.

An increased incidence of malformed fetuses (various craniofacial, appendicular, and visceral defects) and decreased fetal weights were observed following oral administration of 100 mg/kg/day to pregnant rats during the period of organogenesis. This dose is approximately 16 times the maximum recommended human dose (MRHD) of 56 mg/day, based on body surface area (mg/m^2). Maternal toxicity (transient weight loss/reduced maternal weight gain during gestation) was associated with this dose, but there is no evidence to suggest that the teratogenic effects were secondary to the maternal effects. No adverse maternal or embryo-fetal effects were seen at a dose of 20 mg/kg/day (3 times the MRHD on a mg/m^2 basis).

Decreased maternal weight gain, increased resorption of embryos and increased incidences of fetal variations, but not malformations, were observed when pregnant rabbits were given 25 mg/kg/day (8 times the MRHD on a mg/m^2 basis) during organogenesis. The no effect level for maternal and embryo-fetal toxicity in rabbits was 5 mg/kg/day (equivalent to the MRHD on a mg/m^2 basis).

When female rats were given tiagabine 100 mg/kg/day during late gestation and throughout parturition and lactation, decreased maternal weight gain during gestation, an increase in stillbirths, and decreased postnatal offspring viability and growth were found. There are no adequate and well-controlled studies in pregnant women. Tiagabine should be used during pregnancy only if clearly needed.

To provide additional information regarding the effects of in utero exposure to GABITRIL, physicians are advised to recommend that pregnant patients taking GABITRIL enroll in the NAAED Pregnancy Registry. This can be done by calling the toll free number 1-888-233-2334, and must be done by patients themselves. Information on the registry can also be found at the website http://www.aedpregnancyregistry.org/.

Use in Nursing Mothers:

Studies in rats have shown that tiagabine HCl and/or its metabolites are excreted in the milk of that species. Levels of excretion of tiagabine and/or its metabolites in human milk have not been determined and effects on the nursing infant are unknown. GABITRIL should be used in women who are nursing only if the benefits clearly outweigh the risks.

Pediatric Use:

Safety and effectiveness in pediatric patients below the age of 12 have not been established. The pharmacokinetics of tiagabine were evaluated in pediatric patients age 3 to 10 years (see CLINICAL PHARMACOLOGY, Special Populations, Pediatric).

Geriatric Use:

Because few patients over the age of 65 (approximately 20) were exposed to GABITRIL during its clinical evaluation, no specific statements about the safety or effectiveness of GABITRIL in this age group could be made.

ADVERSE REACTIONS

The most commonly observed adverse events in placebo-controlled, parallel-group, add-on epilepsy trials associated with the use of GABITRIL in combination with other antiepilepsy drugs not seen at an equivalent frequency among placebo-treated patients were dizziness/light-headedness, asthenia/lack of energy, somnolence, nausea, nervousness/irritability, tremor, abdominal pain, and thinking abnormal/difficulty with concentration or attention.

Approximately 21% of the 2531 patients who received GABITRIL in clinical trials of epilepsy discontinued treatment because of an adverse event. The adverse events most commonly associated with discontinuation were dizziness (1.7%), somnolence (1.6%), depression (1.3%), confusion (1.1%), and asthenia (1.1%).

In Studies 1 and 2 (U.S. studies), the double-blind, placebo-controlled, parallel-group, add-on studies, the proportion of patients who discontinued treatment because of adverse events was 11% for the group treated with GABITRIL and 6% for the placebo group. The most common adverse events considered the primary reason for discontinuation were confusion (1.2%), somnolence (1.0%), and ataxia (1.0%).

Adverse Event Incidence in Controlled Clinical Trials: Table 5 lists treatment-emergent signs and symptoms that occurred in at least 1% of patients treated with GABITRIL for epilepsy participating in parallel-group, placebo-controlled trials and were numerically more common in the GABITRIL group. In these studies, either GABITRIL or placebo was added to the patient’s current antiepilepsy drug therapy. Adverse events were usually mild or moderate in intensity.

The prescriber should be aware that these figures, obtained when GABITRIL was added to concurrent antiepilepsy drug therapy, cannot be used to predict the frequency of adverse events in the course of usual medical practice when patient characteristics and other factors may differ from those prevailing during clinical studies. Similarly, the cited frequencies cannot be directly compared with figures obtained from other clinical investigations involving different treatments, uses, or investigators. An inspection of these frequencies, however, does provide the prescribing physician with one basis to estimate the relative contribution of drug and non-drug factors to the adverse event incidences in the population studied.

Table 5: Treatment-Emergent Adverse Event [Patients in these add-on studies were receiving one to three concomitant enzyme-inducing antiepilepsy drugs in addition to GABITRIL or placebo. Patients may have reported multiple adverse experiences; thus, patients may be included in more than one category.] Incidence in Parallel-Group, Placebo-Controlled, Add-On Trials (events in at least 1% of patients treated with GABITRIL and numerically more frequent than in the placebo group)
Body System/; COSTART | GABITRIL; N=494; % | Placebo; N=275; %
Body as a Whole
Abdominal Pain | 7 | 3
Pain (unspecified) | 5 | 3
Cardiovascular
Vasodilation | 2 | 1
Digestive
Nausea | 11 | 9
Diarrhea | 7 | 3
Vomiting | 7 | 4
Increased Appetite | 2 | 0
Mouth Ulceration | 1 | 0
Musculoskeletal
Myasthenia | 1 | 0
Nervous System
Dizziness | 27 | 15
Asthenia | 20 | 14
Somnolence | 18 | 15
Nervousness | 10 | 3
Tremor | 9 | 3
Difficulty with Concentration/Attention [COSTART term substituted with a more clinically descriptive term.] | 6 | 2
Insomnia | 6 | 4
Ataxia | 5 | 3
Confusion | 5 | 3
Speech Disorder | 4 | 2
Difficulty with Memory | 4 | 3
Paresthesia | 4 | 2
Depression | 3 | 1
Emotional Lability | 3 | 2
Abnormal Gait | 3 | 2
Hostility | 2 | 1
Nystagmus | 2 | 1
Language Problems | 2 | 0
Agitation | 1 | 0
Respiratory System
Pharyngitis | 7 | 4
Cough Increased | 4 | 3
Skin and Appendages
Rash | 5 | 4
Pruritus | 2 | 0

Other events reported by 1% or more of patients treated with GABITRIL but equally or more frequent in the placebo group were: accidental injury, chest pain, constipation, flu syndrome, rhinitis, anorexia, back pain, dry mouth, flatulence, ecchymosis, twitching, fever, amblyopia, conjunctivitis, urinary tract infection, urinary frequency, infection, dyspepsia, gastroenteritis, nausea and vomiting, myalgia, diplopia, headache, anxiety, acne, sinusitis, and incoordination.

Study 1 was a dose-response study including doses of 32 mg and 56 mg. Table 6 shows adverse events reported at a rate of ≥ 5% in at least one GABITRIL group and more frequent than in the placebo group. Among these events, depression, tremor, nervousness, difficulty with concentration/attention, and perhaps asthenia exhibited a positive relationship to dose.

Table 6: Treatment-Emergent Adverse Event Incidence in Study 1 [Patients in this study were receiving one to three concomitant enzyme-inducing antiepilepsy drugs in addition to GABITRIL or placebo. Patients may have reported multiple adverse experiences; thus, patients may be included in more than one category.] (events in at least 5% of patients treated with GABITRIL 32 or 56 mg and numerically more frequent than in the placebo group)
Body System/; COSTART Term | GABITRIL; 56 mg; (N=57); % | GABITRIL; 32 mg; (N=88); % | Placebo; (N=91); %
Body as a Whole
Accidental Injury | 21 | 15 | 20
Infection | 19 | 10 | 12
Flu Syndrome | 9 | 6 | 3
Pain | 7 | 2 | 3
Abdominal Pain | 5 | 7 | 4
Digestive System
Diarrhea | 2 | 10 | 6
Hemic and Lymphatic System
Ecchymosis | 0 | 6 | 1
Musculoskeletal System
Myalgia | 5 | 2 | 3
Nervous System
Dizziness | 28 | 31 | 12
Asthenia | 23 | 18 | 15
Tremor | 21 | 14 | 1
Somnolence | 19 | 21 | 17
Nervousness | 14 | 11 | 6
Difficulty with Concentration/Attention [COSTART term substituted with a more clinically descriptive term.] | 14 | 7 | 3
Ataxia | 9 | 6 | 6
Depression | 7 | 1 | 0
Insomnia | 5 | 6 | 3
Abnormal Gait | 5 | 5 | 3
Hostility | 5 | 5 | 2
Respiratory System
Pharyngitis | 7 | 8 | 6
Special Senses
Amblyopia | 4 | 9 | 8
Urogenital System
Urinary Tract Infection | 5 | 0 | 2

The effects of GABITRIL in relation to those of placebo on the incidence of adverse events and the types of adverse events reported were independent of age, weight, and gender. Because only 10% of patients were non-Caucasian in parallel-group, placebo-controlled trials, there is insufficient data to support a statement regarding the distribution of adverse experience reports by race.

Other Adverse Events Observed During All Clinical Trials: GABITRIL has been administered to 2531 patients during all phase 2/3 clinical trials, only some of which were placebo-controlled. During these trials, all adverse events were recorded by the clinical investigators using terminology of their own choosing. To provide a meaningful estimate of the proportion of individuals having adverse events, similar types of events were grouped into a smaller number of standardized categories using modified COSTART dictionary terminology. These categories are used in the listing below. The frequencies presented represent the proportion of the 2531 patients exposed to GABITRIL who experienced events of the type cited on at least one occasion while receiving GABITRIL. All reported events are included except those already listed above, events seen only three times or fewer (unless potentially important), events very unlikely to be drug-related, and those too general to be informative. Events are included without regard to determination of a causal relationship to tiagabine.

Events are further classified within body system categories and enumerated in order of decreasing frequency using the following definitions: frequent adverse events are defined as those occurring in at least 1/100 patients; infrequent adverse events are those occurring in 1/100 to 1/1000 patients; rare events are those occurring in fewer than 1/1000 patients.

Body as a Whole: Frequent: Allergic reaction, chest pain, chills, cyst, neck pain, and malaise. Infrequent: Abscess, cellulitis, facial edema, halitosis, hernia, neck rigidity, neoplasm, pelvic pain, photosensitivity reaction, sepsis, sudden death, and suicide attempt.

Cardiovascular System: Frequent: Hypertension, palpitation, syncope, and tachycardia. Infrequent: Angina pectoris, cerebral ischemia, electrocardiogram abnormal, hemorrhage, hypotension, myocardial infarct, pallor, peripheral vascular disorder, phlebitis, postural hypotension, and thrombophlebitis.

Digestive System: Frequent: Gingivitis and stomatitis. Infrequent: Abnormal stools, cholecystitis, cholelithiasis, dysphagia, eructation, esophagitis, fecal incontinence, gastritis, gastrointestinal hemorrhage, glossitis, gum hyperplasia, hepatomegaly, increased salivation, liver function tests abnormal, melena, periodontal abscess, rectal hemorrhage, thirst, tooth caries, and ulcerative stomatitis.

Endocrine System: Infrequent: Goiter and hypothyroidism.

Hemic and Lymphatic System: Frequent: Lymphadenopathy. Infrequent: Anemia, erythrocytes abnormal, leukopenia, petechia, and thrombocytopenia.

Metabolic and Nutritional: Frequent: Edema, peripheral edema, weight gain, and weight loss. Infrequent: Dehydration, hypercholesteremia, hyperglycemia, hyperlipemia, hypoglycemia, hypokalemia, and hyponatremia.

Musculoskeletal System: Frequent: Arthralgia. Infrequent: Arthritis, arthrosis, bursitis, generalized spasm, and tendinous contracture.

Nervous System: Frequent: Depersonalization, dysarthria, euphoria, hallucination, hyperkinesia, hypertonia, hypesthesia, hypokinesia, hypotonia, migraine, myoclonus, paranoid reaction, personality disorder, reflexes decreased, stupor, twitching, and vertigo. Infrequent: Abnormal dreams, apathy, choreoathetosis, circumoral paresthesia, CNS neoplasm, coma, delusions, dry mouth, dystonia, encephalopathy, hemiplegia, leg cramps, libido increased, libido decreased, movement disorder, neuritis, neurosis, paralysis, peripheral neuritis, psychosis, reflexes increased, and urinary retention.

Respiratory System: Frequent: Bronchitis, dyspnea, epistaxis, and pneumonia. Infrequent: Apnea, asthma, hemoptysis, hiccups, hyperventilation, laryngitis, respiratory disorder, and voice alteration.

Skin and Appendages: Frequent: Alopecia, dry skin, and sweating. Infrequent: Contact dermatitis, eczema, exfoliative dermatitis, furunculosis, herpes simplex, herpes zoster, hirsutism, maculopapular rash, psoriasis, skin benign neoplasm, skin carcinoma, skin discolorations, skin nodules, skin ulcer, subcutaneous nodule, urticaria, and vesiculobullous rash.

Special Senses: Frequent: Abnormal vision, ear pain, otitis media, and tinnitus. Infrequent: Blepharitis, blindness, deafness, eye pain, hyperacusis, keratoconjunctivitis, otitis externa, parosmia, photophobia, taste loss, taste perversion, and visual field defect.

Urogenital System: Frequent: Dysmenorrhea, dysuria, metrorrhagia, urinary incontinence, and vaginitis. Infrequent: Abortion, amenorrhea, breast enlargement, breast pain, cystitis, fibrocystic breast, hematuria, impotence, kidney failure, menorrhagia, nocturia, papanicolaou smear suspicious, polyuria, pyelonephritis, salpingitis, urethritis, urinary urgency, and vaginal hemorrhage.

Postmarketing Reports

The following adverse reactions have been identified during postapproval use of GABITRIL. Because these reactions are reported voluntarily from a population of uncertain size, it is not always possible to reliably estimate their frequency or establish a causal relationship to drug exposure.

Skin and subcutaneous tissue disorders: bullous dermatitis

Eye disorders: vision blurred

DRUG ABUSE AND DEPENDENCE

The abuse and dependence potential of GABITRIL have not been evaluated in human studies.

OVERDOSAGE

Human Overdose Experience: Human experience of acute overdose with GABITRIL is limited. Eleven patients in clinical trials took single doses of GABITRIL up to 800 mg. All patients fully recovered, usually within one day. The most common symptoms reported after overdose included somnolence, impaired consciousness, agitation, confusion, speech difficulty, hostility, depression, weakness, and myoclonus. One patient who ingested a single dose of 400 mg experienced generalized tonic-clonic status epilepticus, which responded to intravenous phenobarbital.

From post-marketing experience, reports of overdose involving GABITRIL alone have included cases in which patients required intubation and ventilatory support as part of the management of their status epilepticus. Overdoses involving multiple drugs, including GABITRIL, have resulted in fatal outcomes.Symptoms most often accompanying GABITRIL overdose, alone or in combination with other drugs, have included: seizures including status epilepticus in patients with and without underlying seizure disorders, nonconvulsive status epilepticus, respiratory arrest, coma, loss of consciousness, ataxia, dizziness, confusion, somnolence, drowsiness, impaired speech, aggression, agitation, lethargy, myoclonus, spike wave stupor, encephalopathy, amnesia, dyskinesia, tremors, disorientation, psychotic disorder, vomiting, hostility, and temporary paralysis. Respiratory depression was seen in a number of patients, including children, in the context of seizures.

Management of Overdose: There is no specific antidote for overdose with GABITRIL. If indicated, elimination of unabsorbed drug should be achieved by emesis or gastric lavage; usual precautions should be observed to maintain the airway. General supportive care of the patient is indicated including monitoring of vital signs and observation of clinical status of the patient. Since tiagabine is mostly metabolized by the liver and is highly protein bound, dialysis is unlikely to be beneficial. A Certified Poison Control Center should be consulted for up to date information on the management of overdose with GABITRIL.

DOSAGE AND ADMINISTRATION

General:

The blood level of tiagabine obtained after a given dose depends on whether the patient also is receiving a drug that induces the metabolism of tiagabine. The presence of an inducer means that the attained blood level will be substantially reduced. Dosing should take the presence of concomitant medications into account.

GABITRIL (tiagabine HCl) is recommended as adjunctive therapy for the treatment of partial seizures in patients 12 years and older.

The following dosing recommendations apply to all patients taking GABITRIL:

- GABITRIL is given orally and should be taken with food.
- Do not use a loading dose of GABITRIL.
- Dose titration: Rapid escalation and/or large dose increments of GABITRIL should not be used.
- Missed dose(s): If the patient forgets to take the prescribed dose of GABITRIL at the scheduled time, the patient should not attempt to make up for the missed dose by increasing the next dose. If a patient has missed multiple doses, patient should refer back to his or her physician for possible re-titration as clinically indicated.
- Dosage adjustment of GABITRIL should be considered whenever a change in patient’s enzyme-inducing status occurs as a result of the addition, discontinuation, or dose change of the enzyme-inducing agent.

Induced Adults and Adolescents 12 Years or Older: The following dosing recommendations apply to patients who are already taking enzyme-inducing antiepilepsy drugs (AEDs) (e.g., carbamazepine, phenytoin, primidone, and phenobarbital). Such patients are considered induced patients when administering GABITRIL.

In adolescents 12 to 18 years old, GABITRIL should be initiated at 4 mg once daily. Modification of concomitant antiepilepsy drugs is not necessary, unless clinically indicated. The total daily dose of GABITRIL may be increased by 4 mg at the beginning of Week 2. Thereafter, the total daily dose may be increased by 4 to 8 mg at weekly intervals until clinical response is achieved or up to 32 mg/day. The total daily dose should be given in divided doses two to four times daily. Doses above 32 mg/day have been tolerated in a small number of adolescent patients for a relatively short duration.

In adults, GABITRIL should be initiated at 4 mg once daily. Modification of concomitant antiepilepsy drugs is not necessary, unless clinically indicated. The total daily dose of GABITRIL may be increased by 4 to 8 mg at weekly intervals until clinical response is achieved or, up to 56 mg/day. The total daily dose should be given in divided doses two to four times daily. Doses above 56 mg/day have not been systematically evaluated in adequate and well-controlled clinical trials.

Experience is limited in patients taking total daily doses above 32 mg/day using twice daily dosing. A typical dosing titration regimen for patients taking enzyme-inducing AEDs (induced patients) is provided in Table 7.

Table 7: Typical Dosing Titration Regimen for Patients Already Taking Enzyme-Inducing AEDs
 | Initiation and Titration Schedule | Total Daily Dose
Week 1 | Initiate at 4 mg once daily | 4 mg/day
Week 2 | Increase total daily dose by 4 mg | 8 mg/day; (in two divided doses)
Week 3 | Increase total daily dose by 4 mg | 12 mg/day; (in three divided doses)
Week 4 | Increase total daily dose by 4 mg | 16 mg/day; (in two to four divided doses)
Week 5 | Increase total daily dose by 4 to 8 mg | 20 to 24 mg/day; (in two to four divided doses)
Week 6 | Increase total daily dose by 4 to 8 mg | 24 to 32 mg/day; (in two to four divided doses)
Usual Adult Maintenance Dose in Induced Patients: | 32 to 56 mg/day in two to four divided doses

Non-Induced Adults and Adolescents 12 Years or Older: The following dosing recommendations apply to patients who are taking only non-enzyme-inducing AEDs. Such patients are considered non-induced patients:

Following a given dose of GABITRIL, the estimated plasma concentration in the non-induced patients is more than twice that in patients receiving enzyme-inducing agents. Use in non-induced patients requires lower doses of GABITRIL. These patients may also require a slower titration of GABITRIL compared to that of induced patients (see CLINICAL PHARMACOLOGY, Pharmacokinetics and PRECAUTIONS, General, Use in Non-Induced Patients).

HOW SUPPLIED

Product: 68151-4235

NDC: 68151-4235-3 1 TABLET, FILM COATED in a PACKAGE

ANIMAL TOXICOLOGY

In repeat dose toxicology studies, dogs receiving daily oral doses of 5 mg/kg/day or greater experienced unexpected CNS effects throughout the study. These effects occurred acutely and included marked sedation and apparent visual impairment which was characterized by a lack of awareness of objects, failure to fix on and follow moving objects, and absence of a blink reaction. Plasma exposures (AUCs) at 5 mg/kg/day were equal to those in humans receiving the maximum recommended daily human dose of 56 mg/day. The effects were reversible upon cessation of treatment and were not associated with any observed structural abnormality. The implications of these findings for humans are unknown.

GAB-014

Revised: November 2015

Distributed by:

Teva Pharmaceuticals USA, Inc.

North Wales, PA 19454

GABITRIL is a trademark of Cephalon, Inc., or its affiliates.

©1997-2015 Cephalon, Inc., a wholly-owned subsidiary of Teva Pharmaceutical Industries Ltd. All rights reserved.

U.S. Patent Nos. 5,354,760; 5,866,590; 5,958,951

Printed in U.S.A.

Medication Guide

GABITRIL® (găb-ĭ-trĭl)

(tiagabine hydrochloride)

Tablets

Read this Medication Guide before you start taking GABITRIL and each time you get a refill. There may be new information. This information does not take the place of talking to your healthcare provider about your medical condition or treatment.

What is the most important information I should know about GABITRIL?

Do not stop taking GABITRIL without first talking to your healthcare provider.

Stopping GABITRIL suddenly can cause serious problems.

GABITRIL can cause serious side effects, including:

1. GABITRIL may cause seizures in people who do not have epilepsy. If you do not have a seizure disorder and you take GABITRIL, you may have a seizure or seizures that do not stop (status epilepticus). Call your healthcare provider right away if you have a seizure and you are not taking GABITRIL for epilepsy.

2. Like other antiepileptic drugs, GABITRIL may cause suicidal thoughts or actions in a very small number of people, about 1 in 500. Call a healthcare provider right away if you have any of these symptoms, especially if they are new, worse, or worry you:

- thoughts about suicide or dying
- attempts to commit suicide
- new or worse depression
- new or worse anxiety
- feeling agitated or restless
- panic attacks
- trouble sleeping (insomnia)

- new or worse irritability
- acting aggressive, being angry, or violent
- acting on dangerous impulses
- an extreme increase in activity and talking (mania)
- other unusual changes in behavior or mood

Suicidal thoughts or actions can be caused by things other than medicines. If you have suicidal thoughts or actions, your healthcare provider may check for other causes.
How can I watch for early symptoms of suicidal thoughts and actions?
- Pay attention to any changes, especially sudden changes, in mood, behaviors, thoughts, or feelings.
- Keep all follow-up visits with your healthcare provider as scheduled.
- Call your healthcare provider between visits as needed, especially if you are worried about symptoms.
Do not stop GABITRIL without first talking to a healthcare provider.
- Stopping GABITRIL suddenly can cause serious problems. If you have epilepsy and stop a seizure medicine suddenly, you may have more frequent seizures or seizures that will not stop (status epilepticus).

What is GABITRIL?

GABITRIL is a prescription medicine used with other medicines to treat partial seizures in adults and children age 12 and older.

Who should not take GABITRIL?

Do not take GABITRIL if you are allergic to tiagabine hydrochloride or any of the other ingredients in GABITRIL. See the end of this Medication Guide for a complete list of ingredients in GABITRIL.

What should I tell my healthcare provider before taking GABITRIL?

Before taking GABITRIL, tell your healthcare provider if you:

- have or have had depression, mood problems, or suicidal thoughts or behavior
- have liver problems
- have a history of seizures that do not stop (status epilepticus)
- have any other medical conditions
- are pregnant or plan to become pregnant. It is not known if GABITRIL can harm your unborn baby. Tell your healthcare provider right away if you become pregnant while taking GABITRIL. You and your healthcare provider will decide if you should take GABITRIL while you are pregnant.
  - If you become pregnant while taking GABITRIL, talk to your healthcare provider about registering with the North American Antiepileptic Drug (NAAED) Pregnancy Registry. The purpose of this registry is to collect information about the safety of antiepileptic medicines during pregnancy. You can enroll in this registry by calling 1-888-233-2334.
- are breastfeeding or plan to breastfeed. It is not known if GABITRIL passes into breast milk or if it can harm your baby. Talk to your healthcare provider about the best way to feed your baby if you take GABITRIL.

Tell your healthcare provider about all the medicines you take, including prescription and non-prescription medicines, vitamins, and herbal supplements. Taking GABITRIL with certain other medicines can cause side effects or affect how well they work. Do not start or stop other medicines without talking to your healthcare provider.

Know the medicines you take. Keep a list of them and show it to your healthcare provider and pharmacist when you get a new medicine. Always tell your healthcare provider if there are any changes in any other medicines that you take.

How should I take GABITRIL?

- Take GABITRIL exactly as your healthcare provider tells you.
- Your healthcare provider may change your dose.
- GABITRIL should be taken with food.
- Do not stop taking GABITRIL without talking to your healthcare provider.
Stopping GABITRIL suddenly can increase your chances of having a seizure or cause seizures that will not stop.
- If you miss a dose of GABITRIL, do not take 2 doses of GABITRIL at the same time. Contact your healthcare provider if you miss more than one dose.

If you take too much GABITRIL, call your healthcare provider or local Poison Control Center right away.

What should I avoid while taking GABITRIL?

- Do not drink alcohol or take other medicines that make you sleepy or dizzy while taking GABITRIL without first talking to your healthcare provider. Taking GABITRIL with alcohol or drugs that cause sleepiness or dizziness may make your sleepiness or dizziness worse.
- Do not drive, operate heavy machinery, or do other dangerous activities until you know how GABITRIL affects you. GABITRIL can slow your thinking and motor skills.

What are possible side effects of GABITRIL?

See “What is the most important information I should know about GABITRIL?”

GABITRIL may cause other serious side effects including:

- seizures that can happen more often or become worse
- trouble concentrating, problems with speech and language, feeling confused, feeling sleepy and tired, and problems thinking
- weakness all over your body
- eye and vision problems
- serious rash

Call your healthcare provider right away if you have any of the serious side effects listed above.

The most common side effects of GABITRIL include:

- dizziness
- lack of energy
- drowsiness
- nausea
- nervousness
- tremor
- stomach pain
- abnormal thinking
- difficulty with concentration or attention

These are not all the possible side effects of GABITRIL. For more information, ask your healthcare provider or pharmacist. Tell your healthcare provider if you have any side effect that bothers you or that does not go away.

Call your doctor for medical advice about side effects. You may report side effects to FDA at 1-800-FDA-1088.

How should I store GABITRIL?

- Store GABITRIL between 68°F to 77°F (20°C to 25°C)
- Keep GABITRIL out of light
- Keep GABITRIL dry

Keep GABITRIL and all medicines out of the reach of children.

General Information about GABITRIL

Medicines are sometimes prescribed for purposes other than those listed in a Medication Guide. Do not use GABITRIL for a condition for which it was not prescribed. Do not give GABITRIL to other people, even if they have the same symptoms that you have. It may harm them.

This Medication Guide summarizes the most important information about GABITRIL. If you would like more information, talk with your healthcare provider. You can ask your pharmacist or healthcare provider for information about GABITRIL that is written for health professionals.

For more information, go to www.GABITRIL.com or call 1-800-896-5855.

What are the ingredients in GABITRIL?

Active Ingredient: tiagabine hydrochloride

Inactive Ingredients: ascorbic acid, colloidal silicon dioxide, crospovidone, hydrogenated vegetable oil wax, hydroxypropyl cellulose, hypromellose, lactose, magnesium stearate, microcrystalline cellulose, pregelatinized starch, stearic acid and titanium dioxide.

In addition:

- the 2 mg tablets contain FD&C Yellow No. 6
- the 4 mg tablets contain D&C Yellow No. 10
- the 12 mg tablets contain D&C Yellow No. 10 and FD&C Blue No. 1
- the 16 mg tablets contain FD&C Blue No. 2

This Medication Guide has been approved by the U.S. Food and Drug Administration.

GABMG-002

November 2015

Rx only

Distributed by:

Teva Pharmaceuticals USA, Inc.

North Wales, PA 19454

U.S. Patent Nos. 5,354,760; 5,866,590; 5,958,951

©2015 Cephalon, Inc., a wholly-owned subsidiary of Teva Pharmaceutical Industries Ltd. All rights reserved.

Printed in U.S.A.